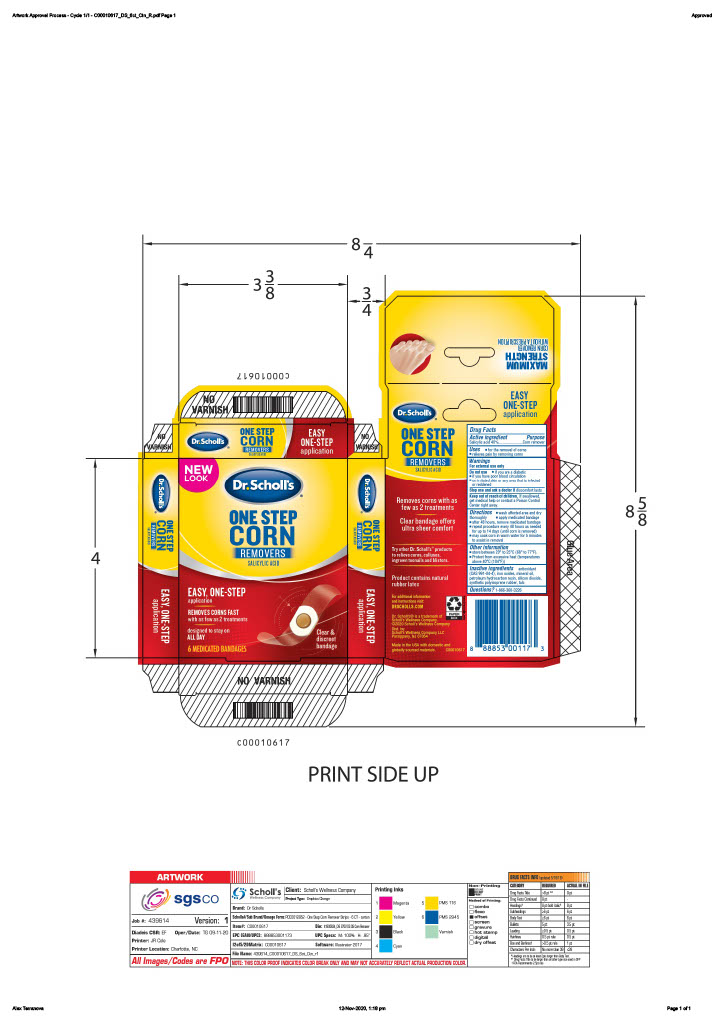 DRUG LABEL: Scholls Wellness Company LLC
NDC: 73469-0753 | Form: DISC
Manufacturer: Scholls Wellness Company LLC
Category: otc | Type: HUMAN OTC DRUG LABEL
Date: 20251221

ACTIVE INGREDIENTS: SALICYLIC ACID 0.4 g/1 g
INACTIVE INGREDIENTS: SILICON DIOXIDE; MINERAL OIL; TALC

(90000084) One Step Corn Removers

Drug Facts

Active Ingredient

Active Ingredient Purpose

Salicylic Acid 40%.......................Corn remover

Purpose

Corn remover

Uses

- for the removal of corns
- relieves pain by removing corns

Warnings

For external use only

Do not use

- if you are a diabetic
- if you have poor blood circulation
- on irritated skin or any area that is infected or reddened

Stop use and ask a doctor if discomfort lasts

Keep out of reach of children. If swallowed,

get medical help or contact a Poison Control Center right away.

Directions

- wash affected area and dry thoroughly
- apply medicated bandage
- after 48 hours, remove medicated bandage
- repeat procedure every 48 hours as needed for up to 14 days (until corn is removed)
- may soak corn in warm water for 5 minutes to assist removal

Other information

- store between 20ºC to 25ºC (68º to 77ºF).
- Protect from excessive heat (temperatures above 40ºC (104ºF))

Inactive ingredients

Inactive ingredients antioxidant

(CAS 991-84-4), iron oxides, mineral oil,

petroleum hydrocarbon resin, silicon dioxide,

synthetic polyisoprene rubber, talc

Questions

Questions? 1-866-360-3226